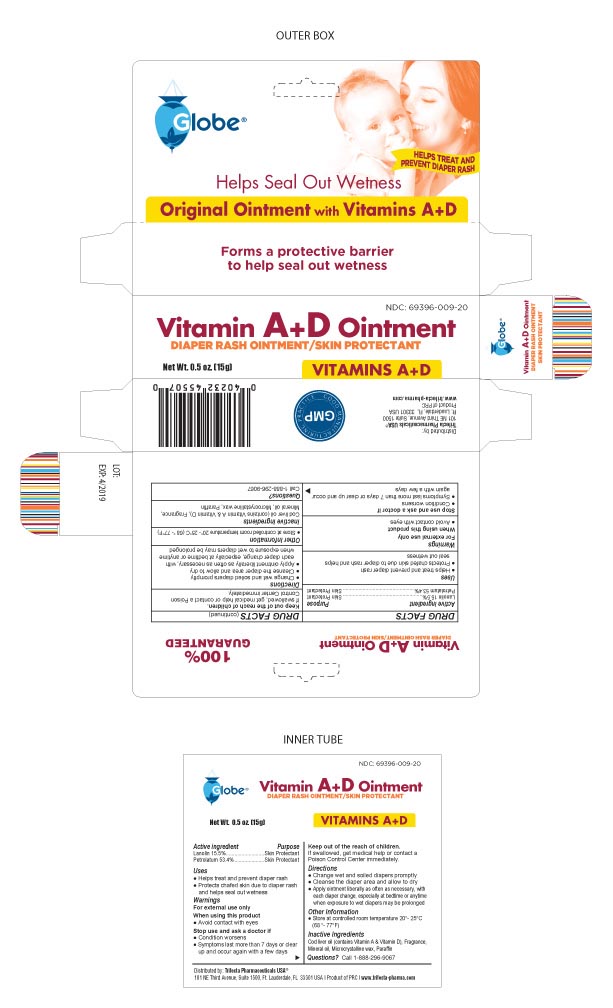 DRUG LABEL: Vitamin A and D
NDC: 69396-009 | Form: OINTMENT
Manufacturer: Trifecta Pharmaceuticals USA LLC
Category: otc | Type: HUMAN OTC DRUG LABEL
Date: 20241220

ACTIVE INGREDIENTS: PETROLATUM 53.4 g/100 g; LANOLIN 15.5 g/100 g
INACTIVE INGREDIENTS: MICROCRYSTALLINE WAX; PARAFFIN; COD LIVER OIL; MINERAL OIL

Vitamin A and D Ointment

Active Ingredient

Lanolin 15.5%

Petrolatum 53.4%

Purpose

Skin Protectant

Uses

Helps treat and prevent diaper rash

Protects chafed skin due to diaper rash and helps seal out wetness

Stop use and ask a doctor

Condition worsens

Symptoms last more than 7 days or clear up and occur again with a few days

Keep our of reach of children

If swallowed, get medical help or contact a Poison Control Center immediately

Directions

Change wet and soiled diapers promptly

Cleanse the diaper area and allow to dry

Apply ointment liberally as often as necessary, with each diaper change, especially at bedtime or anytime when exposure to wet diapers may be prolonged.

Inactive Ingredients

Cod liver oil (contains Vitamin A and Vitamin D), Fragrance, Mineral Oil, Microcrystalline Wax, Paraffin

Distributed by

Trifecta Pharmaceuticals USA

101 NE Third Avenue, Suite 1500

Ft. Lauderdale, FL. 33301

Product of PRC

www.trifecta-pharma.com

Warnings

For external use only

When using this product avoid contact with eyes

STORAGE AND HANDLING

Store at controlled room temperature 20º 25ºC (68º-77ºF)

Questions 1-888-296-9067